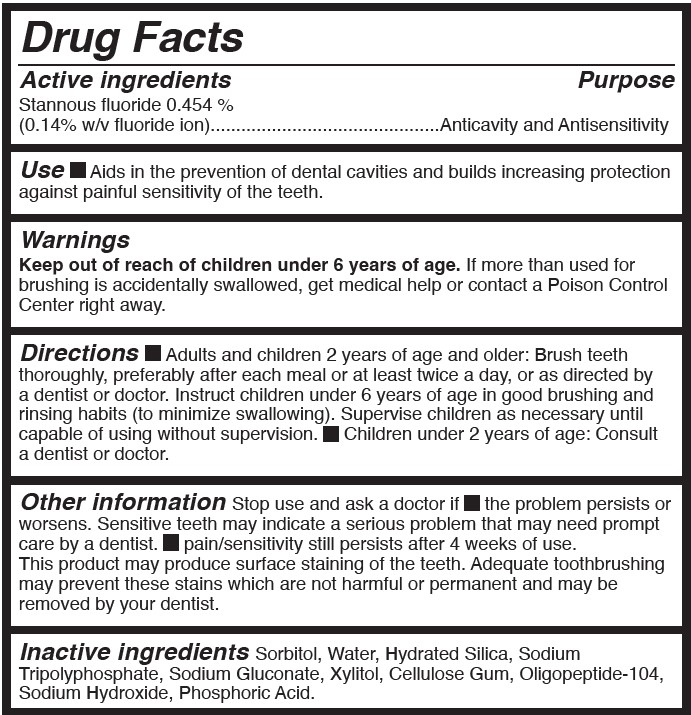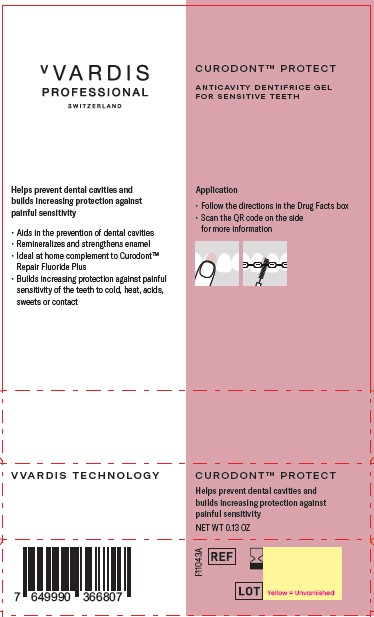 DRUG LABEL: CURODONT PROTECT
NDC: 72247-107 | Form: PASTE, DENTIFRICE
Manufacturer: CREDENTIS AG
Category: otc | Type: HUMAN OTC DRUG LABEL
Date: 20241201

ACTIVE INGREDIENTS: STANNOUS FLUORIDE 0.14 g/100 g
INACTIVE INGREDIENTS: SORBITOL; SODIUM HYDROXIDE; WATER; HYDRATED SILICA; SODIUM TRIPOLYPHOSPHATE; SODIUM GLUCONATE; OLIGOPEPTIDE 104; XYLITOL; CARBOXYMETHYLCELLULOSE SODIUM, UNSPECIFIED; PHOSPHORIC ACID

CREDENTIS - vVardis Professional - CURODONT PROTECT (72247-107)

ACTIVE INGREDIENTS

STANNOUS FLUORIDE 0.454%

(0.14% W/V FLUORIDE ION)

PURPOSE

ANTICAVITY AND ANTISENSITIVITY

USE

- AIDS IN THE PREVENTION OF DENTAL CAVITIES AND BUILDS INCREASING PROTECTION AGAINST PAINFUL SENSITIVITY OF THE TEETH.

WARNINGS

Stop use and ask a doctor if

- the problem persists or worsens. Sensitive teeth may indicate a serious problem that may need prompt care by a dentist.
- pain/sensitivity still persists after 4 weeks of use.

KEEP OUT OF REACH OF CHILDREN. IF MORE THAN USED FOR RINSING IS ACCIDENTALLY SWALLOWED, GET MEDICAL HELP OR CONTACT A POISON CONTROL CENTER RIGHT AWAY.

DIRECTIONS

- Adults and children 2 years of age and older: Brush teeth thoroughly, preferably after each meal or at least twice a day, or as directed by a dentist or doctor. Instruct children under 6 years of age in good brushing and rinsing habits (to minimize swallowing). Supervise children as necessary until capable of using without supervision.
- Children under 2 years of age: Consult a dentist or doctor.

OTHER INFORMATION

This product may produce surface staining of the teeth. Adequate toothbrushing may prevent these stains which are not harmful or permanent and may be removed by your dentist.

INACTIVE INGREDIENTS

Sorbitol, Water, Hydrated Silica, Sodium Tripolyphosphate, Sodium Gluconate, Xylitol, Cellulose Gum, Oligopeptide-104, Sodium Hydroxide, Phosphoric Acid.